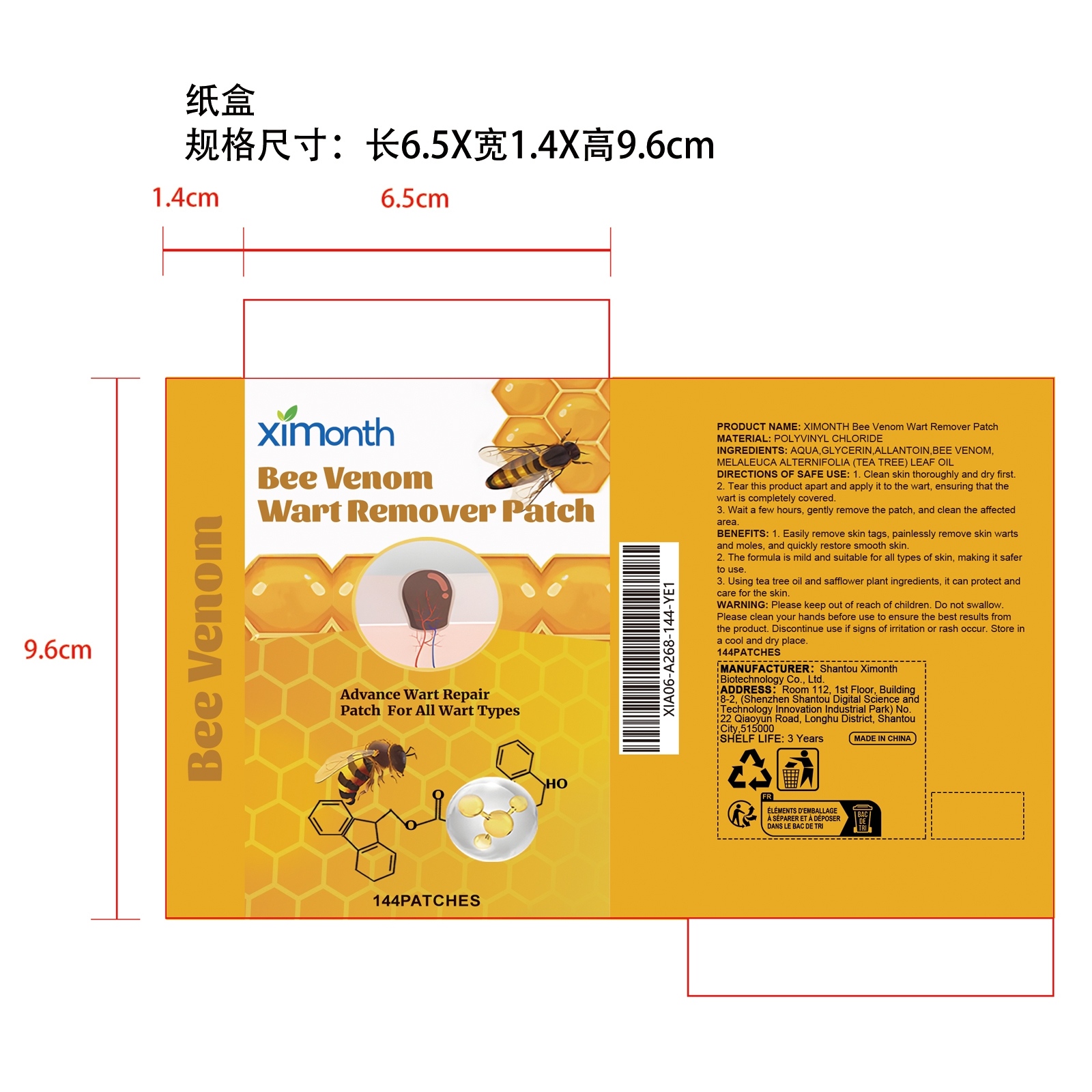 DRUG LABEL: XIMONTH Bee Venom Wart Remover Patch
NDC: 84989-010 | Form: PATCH
Manufacturer: Shantou Ximonth Biotechnology Co., Ltd.
Category: otc | Type: HUMAN OTC DRUG LABEL
Date: 20251126

ACTIVE INGREDIENTS: MELALEUCA ALTERNIFOLIA (TEA TREE) LEAF OIL 0.0288 mg/144 mg
INACTIVE INGREDIENTS: GLYCERIN 7.2 mg/144 mg; ALLANTOIN 0.072 mg/144 mg; APIS MELLIFERA VENOM 0.0288 mg/144 mg; AQUA 136.6704 mg/144 mg

ACTIVE INGREDIENT

MELALEUCA ALTERNIFOLIA (TEA TREE) LEAF OIL

PURPOSE

1. Easily remove skin tags, painlessly remove skin warts and moles, and quickly restore smooth skin.

2. The formula is mild and suitable for all types of skin, making it safer to use.

3. Using tea tree oil and safflower plant ingredients, it can protect and care for the skin.

WHEN USING

1. Clean skin thoroughly and dry first

2. Tear this product apart and apply it to the wart, ensuring that the wart is completely covered

3. Wait a few hours, gently remove the patch, and clean the affected area.

WARNINGS

Please keep out of reach of children. Do not swallow.Please clean your hands before use to ensure the best results from the product. Discontinue use if signs of irritation or rash occur. Store in a cool and dry place.

DO NOT USE

Discontinue use if signs of irritation or rash occur.

STOP USE

Discontinue use if signs of irritation or rash occur.

KEEP OUT OF REACH OF CHILDREN

Please keep out of reach of children. Do not swallow.

STORAGE AND HANDLING

Store in a cool and dry place.

INACTIVE INGREDIENT

AQUA、GLYCERIN、ALLANTOIN、APIS MELLIFERA VENOM

DOSAGE AND ADMINISTRATION

1. Clean skin thoroughly and dry first

2. Tear this product apart and apply it to the wart, ensuring that the wart is completely covered

3. Wait a few hours, gently remove the patch, and clean the affected area.

INDICATIONS AND USAGE

Easily remove skin tags, painlessly remove skin warts and moles, and quickly restore smooth skin.